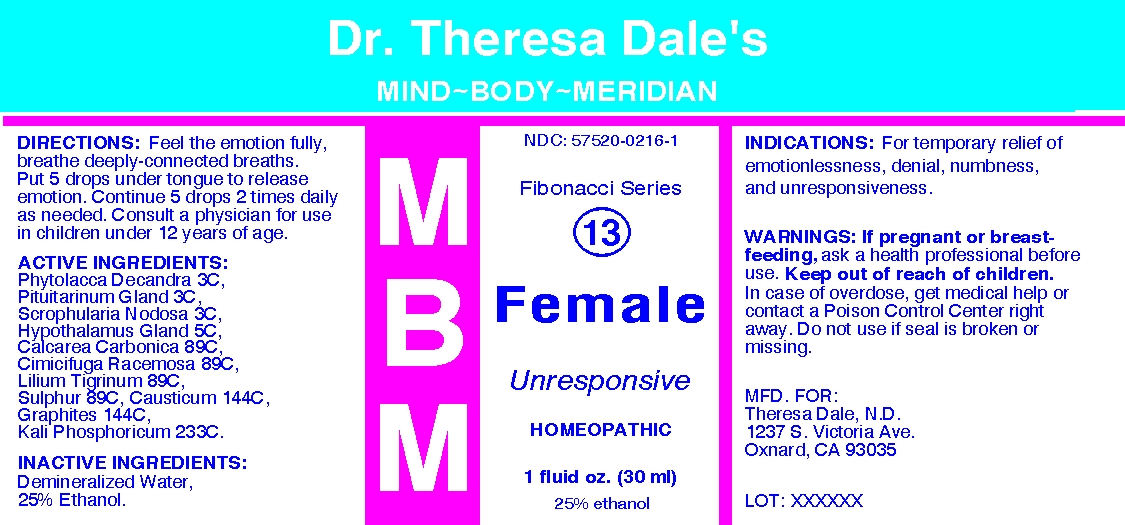 DRUG LABEL: MBM 13 Female
NDC: 57520-0216 | Form: LIQUID
Manufacturer: Apotheca Company
Category: homeopathic | Type: HUMAN OTC DRUG LABEL
Date: 20100719

ACTIVE INGREDIENTS: PHYTOLACCA AMERICANA ROOT 3 [hp_C]/1 mL; SCROPHULARIA NODOSA 3 [hp_C]/1 mL; OYSTER SHELL CALCIUM CARBONATE, CRUDE 89 [hp_C]/1 mL; BLACK COHOSH 89 [hp_C]/1 mL; LILIUM TIGRINUM 89 [hp_C]/1 mL; SULFUR 89 [hp_C]/1 mL; CAUSTICUM 144 [hp_C]/1 mL; GRAPHITE 144 [hp_C]/1 mL; POTASSIUM PHOSPHATE, DIBASIC 233 [hp_C]/1 mL; SUS SCROFA HYPOTHALAMUS 5 [hp_C]/1 mL; SUS SCROFA PITUITARY GLAND 3 [hp_C]/1 mL
INACTIVE INGREDIENTS: WATER; ALCOHOL

MBM 13 Female

ACTIVE INGREDIENT

ACTIVE INGREDIENTS: Phytolacca decandra 3C, Pituitarinum gland 3C, Scrophularia nodosa 3C, Hypothalamus gland 5C, Calcarea carbonica 89C, Cimicifuga racemosa 89C, Lilium tigrinum 89C, Sulphur 89C, Causticum 144C, Graphites 144C, Kali phosphoricum 233C.

PURPOSE

INDICATIONS: For temporary relief of emotionlessness, denial, numbness, and unresponsiveness.

WARNINGS

WARNINGS: If pregnant or breast-feeding, ask a health professional before use.

Keep out of reach of children. In case of overdose, get medical help or contact a Poison Control Center right away. Do not use if seal is broken or missing.

DOSAGE AND ADMINISTRATION

DIRECTIONS: Feel the emotion fully, breathe deeply-connected breaths. Put 5 drops under tongue to release emotion. Continue 5 drops 2 times daily as needed. Consult a physician for use in children under 12 years of age.

INACTIVE INGREDIENTS: Demineralized water, 25% Ethanol

QUESTIONS

MFD. FOR:

Theresa Dale, N.D.

1237 S. Victoria Ave.

Oxnard, CA 93035

PACKAGE LABEL

Dr. Theresa Dale's

MIND-BODY-MERIDIAN

Fibonacci Series

13

Female

Unresponsive

HOMEOPATHIC

1 fluid oz. (30 ml)